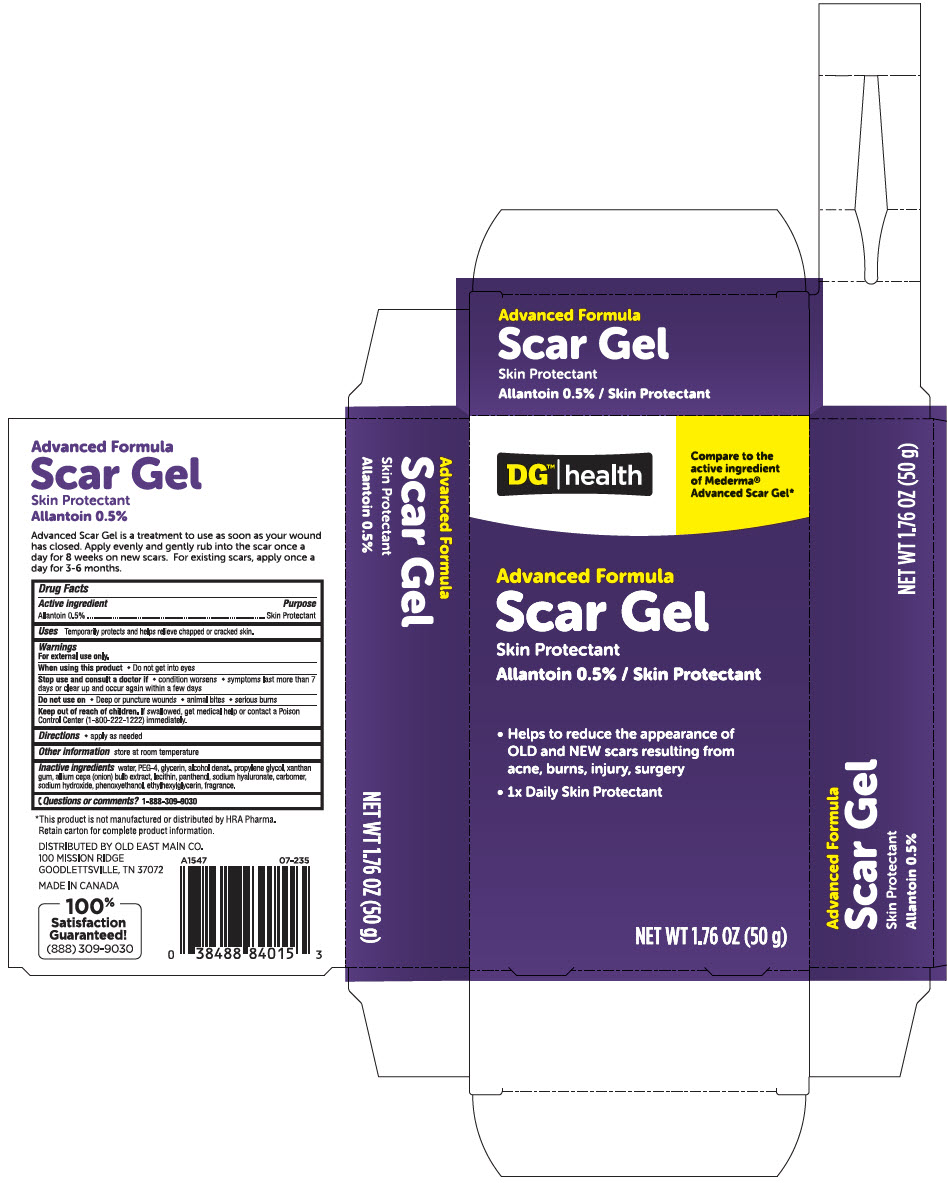 DRUG LABEL: DGH Advanced Formula Scar Skin Protectant
NDC: 55910-540 | Form: GEL
Manufacturer: Dolgencorp Inc
Category: otc | Type: HUMAN OTC DRUG LABEL
Date: 20241108

ACTIVE INGREDIENTS: Allantoin 5 mg/1 g
INACTIVE INGREDIENTS: Water; POLYETHYLENE GLYCOL 200; Glycerin; Alcohol; Propylene Glycol; Xanthan Gum; Onion; LECITHIN, SOYBEAN; Panthenol; HYALURONATE SODIUM; CARBOMER HOMOPOLYMER, UNSPECIFIED TYPE; Sodium Hydroxide; PHENOXYETHANOL; Ethylhexylglycerin

DGH Advanced Formula Scar Gel Skin Protectant

Drug Facts

Active ingredient

Allantoin 0.5%

Purpose

Skin Protectant

Uses

Temporarily protects and helps relieve chapped or cracked skin.

Warnings

For external use only.

When using this product

- Do not get into eyes

Stop use and consult a doctor if

- condition worsens
- symptoms last more than 7 days or clear up and occur again within a few days

Do not use on

- Deep or puncture wounds
- animal bites
- serious burns

Keep out of reach of children. If swallowed, get medical help or contact a Poison Control Center (1-800-222-1222) immediately.

Directions

- apply as needed

Other information

store at room temperature.

Inactive ingredients

water, PEG-4, glycerin, alcohol denat., propylene glycol, xanthan gum, allium cepa (onion) bulk extract, soy lecithin, panthenol, sodium hyaluronate, carbomer, sodium hydroxide, phenoxyethanol, ethylhexylglycerin, fragrance

Questions or comments?

1-888-309-9030

DISTRIBUTED BY OLD EAST MAIN CO.
100 MISSION RIDGE
GOODLETTSVILLE, TN 37072

PRINCIPAL DISPLAY PANEL - 50 g Tube Carton

DG™ | health

Compare to the
active ingredient
of Mederma®
Advanced Scar Gel*

Advanced Formula

Scar Gel

Skin Protectant

Allantoin 0.5% / Skin Protectant

- Helps to reduce the appearance of
  OLD and NEW scars resulting from
  acne, burns, injury, surgery
- 1x Daily Skin Protectant

NET WT 1.76 OZ (50 g)